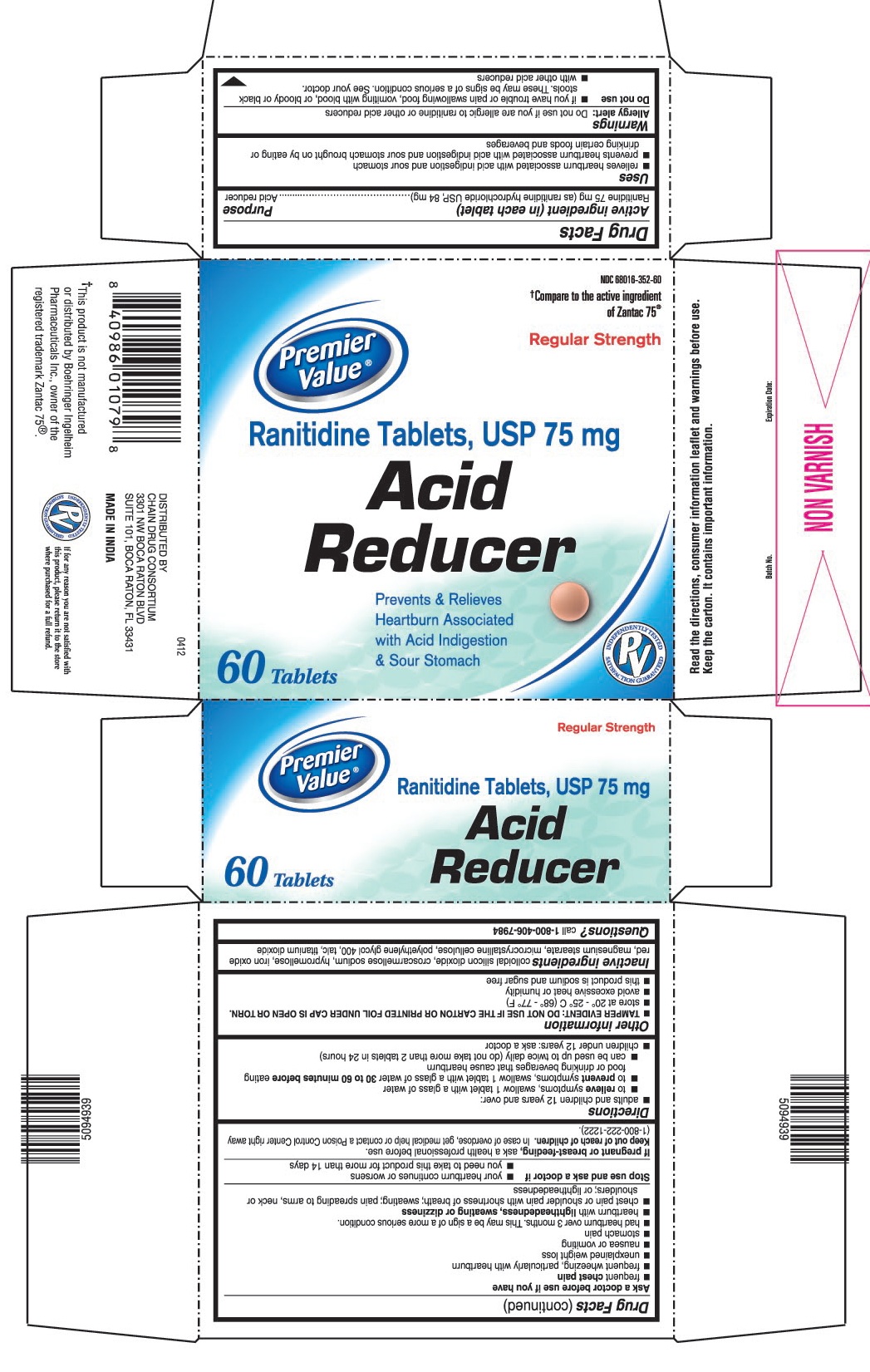 DRUG LABEL: Ranitidine - Acid Reducer
NDC: 68016-352 | Form: TABLET, FILM COATED
Manufacturer: Chain Drug Consortium, LLC.
Category: otc | Type: HUMAN OTC DRUG LABEL
Date: 20151006

ACTIVE INGREDIENTS: RANITIDINE HYDROCHLORIDE 75 mg/1 1
INACTIVE INGREDIENTS: SILICON DIOXIDE; CROSCARMELLOSE SODIUM; HYPROMELLOSES; FERRIC OXIDE RED; MAGNESIUM STEARATE; CELLULOSE, MICROCRYSTALLINE; POLYETHYLENE GLYCOL 400; TALC; TITANIUM DIOXIDE

Drug Facts

ACTIVE INGREDIENT (IN EACH TABLET)

Ranitidine 75 mg (as ranitidine hydrochloride USP, 84 mg)

PURPOSE

Acid reducer

USES

- relieves heartburn associated with acid indigestion and sour stomach
- prevents heartburn associated with acid indigestion and sour stomach brought on by eating or drinking certain foods and beverages

WARNINGS

Allergy alert: Do not use if you are allergic to ranitidine or other acid reducers

Do not use

- if you have trouble or pain swallowing food, vomiting with blood, or bloody or black stools. These may be signs of a serious condition. See your doctor.
- with other acid reducers

Ask a doctor before use if you have

- frequent chest pain
- frequent wheezing, particularly with heartburn
- unexplained weight loss
- nausea or vomiting
- stomach pain
- had heartburn over 3 months. This may be a sign of a more serious condition.
- heartburn with lightheadedness, sweating or dizziness
- chest pain or shoulder pain with shortness of breath; sweating; pain spreading to arms, neck or shoulders; or lightheadedness

Stop use and ask a doctor if

- your heartburn continues or worsens
- you need to take this product for more than 14 days

If pregnant or breast-feeding,

ask a health professional before use.

Keep out of reach of children.

In case of overdose, get medical help or contact a Poison Control Center right away (1-800-222-1222).

DIRECTIONS

- adults and children 12 years and over:
  - to relieve symptoms, swallow 1 tablet with a glass of water
  - to prevent symptoms, swallow 1 tablet with a glass of water 30 to 60 minutes before eating food or drinking beverages that cause heartburn
  - can be used up to twice daily (do not take more than 2 tablets in 24 hours)
- children under 12 years: ask a doctor

OTHER INFORMATION

- TAMPER EVIDENT: DO NOT USE IF THE CARTON OR PRINTED FOIL UNDER CAP IS OPEN OR TORN.
- store at 20° - 25° C (68° - 77° F)
- avoid excessive heat or humidity
- this product is sodium and sugar free

INACTIVE INGREDIENTS

colloidal silicon dioxide, croscarmellose sodium, hypromellose, iron oxide red, magnesium stearate, microcrystalline cellulose, polyethylene glycol 400, talc, titanium dioxide

QUESTIONS?

call 1-800-406-7984

Read the directions, consumer information leaflet and warnings before use.

Keep the carton. It contains important information.

DISTRIBUTED BY

CHAIN DRUG CONSORTIUM

3301 NW BOCA RATON BLVD

SUITE 101, BOCA RATON, FL 33431

PRINCIPAL DISPLAY PANEL

Premier Value®

NDC 68016-352-60

Ranitidine Tablets, USP 75 mg

Acid Reducer

Regular Strength

60 Tablets

Prevents & Relieves Heartburn Associated with Acid Indigestion & Sour Stomach

† Compare to the active ingredient of Zantac 75®

† This product is not manufactured or distributed by Boehringer Ingelheim Pharmaceuticals Inc., owner of the registered trademark Zantac 75®.